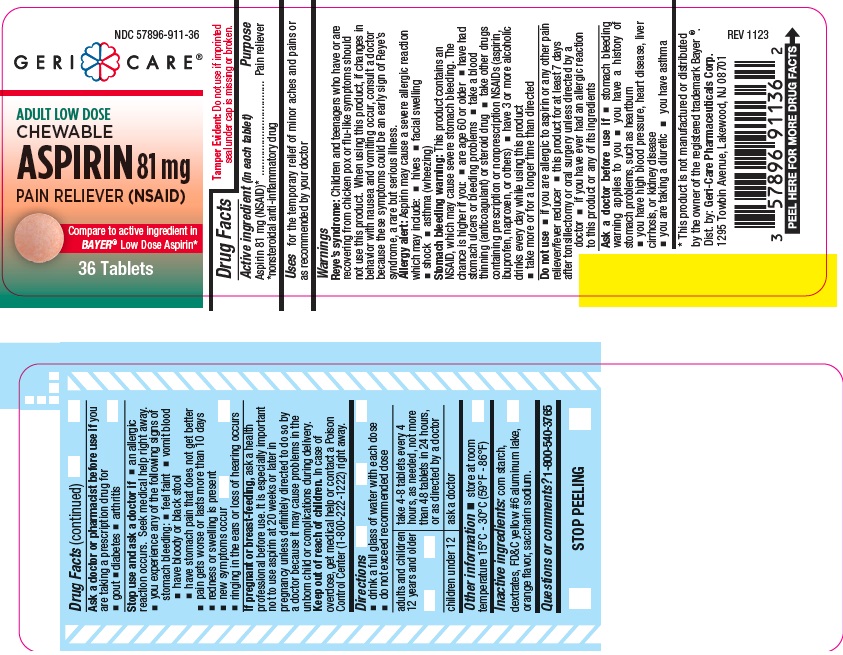 DRUG LABEL: Low Strength Chewable Aspirin
NDC: 57896-911 | Form: TABLET, CHEWABLE
Manufacturer: Geri-Care Pharmaceutical Corp
Category: otc | Type: HUMAN OTC DRUG LABEL
Date: 20241203

ACTIVE INGREDIENTS: ASPIRIN 81 mg/1 1
INACTIVE INGREDIENTS: FD&C YELLOW NO. 6; SACCHARIN SODIUM; DEXTRATES; STARCH, CORN

gc 911

Active ingredient (in each tablet)

Aspirin 81 mg(NSAID)*
*nonsteroidal anti-inflammatory drug

Purpose

Pain reliever

Uses

for the temporary relief of minor aches and pains or as recommended by your doctor

Warnings

Reye's Syndrome: Children and teenagers who have or are recovering from chicken pox or flu-like symptoms should not use this product. When using this product, if changes in behavior with nausea and vomiting occur, consult a doctor because these symptoms could be an early sign of Reye's syndrome, a rare but serious illness.

Allergy Alert: Aspirin may cause a severe allergic reaction which may include:

- hives
- facial swelling
- asthma (wheezing)
- shock

Stomach bleeding warning:

This product contains an NSAID, which may cause severe stomach bleeding. The chance is higher if you:

- are age 60 or older
- have had stomach ulcers or bleeding problems
- take a blood thinning (anticoagulant) or steroid drug
- take other drugs containing prescription or nonprescription NSAIDs (aspirin, ibuprofen, naproxen, or others)
- have 3 or more alcoholic drinks every day while using this product
- take more or for a longer time than directed

Do not use

- if your are allergic to aspirin or any other pain reliever/fever reducer.
- this product for at least 7 days after tonsillectomy or oral surgery unless directed by a doctor
- if you have ever had an allergic reaction to this product or any of its ingredients

Ask a doctor before use if

- the stomach bleeding warning applies to you
- you have a history of stomach problems, such as heartburn
- you have high blood pressure, heart disease, liver cirrhosis, or kidney disease
- you are taking a diuretic
- you have asthma

Ask a doctor or pharmacist before use if you are you
are taking a prescription drug for
 gout diabetes  arthritis

Stop use and ask a doctor if

- you experience any of the following signs of stomach bleeding: -feel faint -vomit blood -have bloody or black stools -have stomach pain that does not get better
- an allergic reaction occurs. Seek medical help right away
- pain gets worse or lasts more than 10 days
- redness or swelling is present
- fever gets worse or lasts more than 3 days
- any new symptoms occur
- ringing in the ears or loss of hearing occurs

If pregnant or breast-feeding,

ask a health professional before use. it is especially important not to use aspirin at 20 weeks or later in
pregnancy unless definitely directed to do so by a doctor because it may cause problems in the unborn child or complications during delivery.

Keep out of reach of children. In case of overdose , get medical help or contact a Poison Control Center (1-800-222-1222) right away.

Directions

- drink a full glass of water with each dose
- do not exceed recommended dose
- adults and children 12 years and older: take 4-8 tablets every 4 hours, as needed, not more than 48 tablets in 24 hours, or as directed by a doctor
- children under 12 years: ask a doctor

Other information

- store at room temperature 15⁰C - 30⁰C (59⁰F - 86⁰F)

Inactive ingredients

corn starch, dextrates, FD&C yellow #6 aluminum lake, orange flavor, saccharin sodium.

Questions or comments?

1-800-540-3765